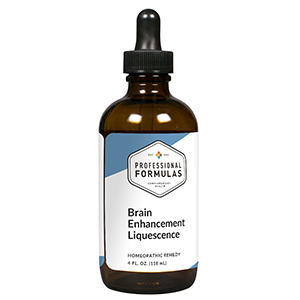 DRUG LABEL: Brain Enhancement Liquescence
NDC: 63083-3006 | Form: LIQUID
Manufacturer: Professional Complementary Health Formulas
Category: homeopathic | Type: HUMAN OTC DRUG LABEL
Date: 20190815

ACTIVE INGREDIENTS: GINKGO 2 [hp_X]/118 mL; COLCHICUM AUTUMNALE BULB 3 [hp_X]/118 mL; SCUTELLARIA LATERIFLORA WHOLE 3 [hp_X]/118 mL; CONVALLARIA MAJALIS 4 [hp_X]/118 mL; NUTMEG 4 [hp_X]/118 mL; AMANITA MUSCARIA FRUITING BODY 6 [hp_X]/118 mL; AMBERGRIS 6 [hp_X]/118 mL; SEMECARPUS ANACARDIUM JUICE 6 [hp_X]/118 mL; BARIUM CARBONATE 6 [hp_X]/118 mL; BOS TAURUS BRAIN 6 [hp_X]/118 mL; .GAMMA.-AMINOBUTYRIC ACID 6 [hp_X]/118 mL; POTASSIUM BROMIDE 6 [hp_X]/118 mL; RIBOFLAVIN 6 [hp_X]/118 mL; LEAD 12 [hp_X]/118 mL; GLYCERIN 16 [hp_X]/118 mL
INACTIVE INGREDIENTS: ALCOHOL; WATER

T6

ACTIVE INGREDIENTS

Ginkgo biloba 2X
Colchicum autumnale 3X
Scutellaria lateriflora 3X
Convallaria majalis 4X
Nux moschata 4X
Agaricus muscarius 6X
Ambra grisea 6X
Anacardium orientale 6X
Baryta carbonica 6X
Brain 6X
GABA 6X
Kali bromatum 6X
Riboflavin 6X
Plumbum metallicum 12X
Glycerinum 16X

QUESTIONS

Professional Formulas

PO Box 2034 Lake Oswego, OR 97035

INDICATIONS

For the temporary relief of weakened memory, absentmindedness, reduced focus or comprehension, confusion, irritability, or occasional headache.*

PURPOSE

*Claims based on traditional homeopathic practice, not accepted medical evidence. Not FDA evaluated.

WARNINGS

Consult a doctor if condition worsens or if symptoms persist. Keep out of the reach of children. In case of overdose, get medical help or contact a poison control center right away. If pregnant or breastfeeding, ask a healthcare professional before use.

Keep out of the reach of children.

PREGNANCY OR BREAST FEEDING

If pregnant or breastfeeding, ask a healthcare professional before use.

DIRECTIONS

Place drops under tongue 30 minutes before/after meals. Adults and children 12 years and over: Take one full dropper up to 2 times per day. Consult a physician for use in children under 12 years of age.

OTHER INFORMATION

Tamper resistant. If seal is broken, do not use. After opening, close container tightly and store at room temperature away from heat.

INACTIVE INGREDIENTS

20% ethanol, purified water.

LABEL

Est 1985

Professional Formulas

Complementary Health

Brain Enhancement Liquescence

Homeopathic Remedy

4 FL. OZ. (118 mL)